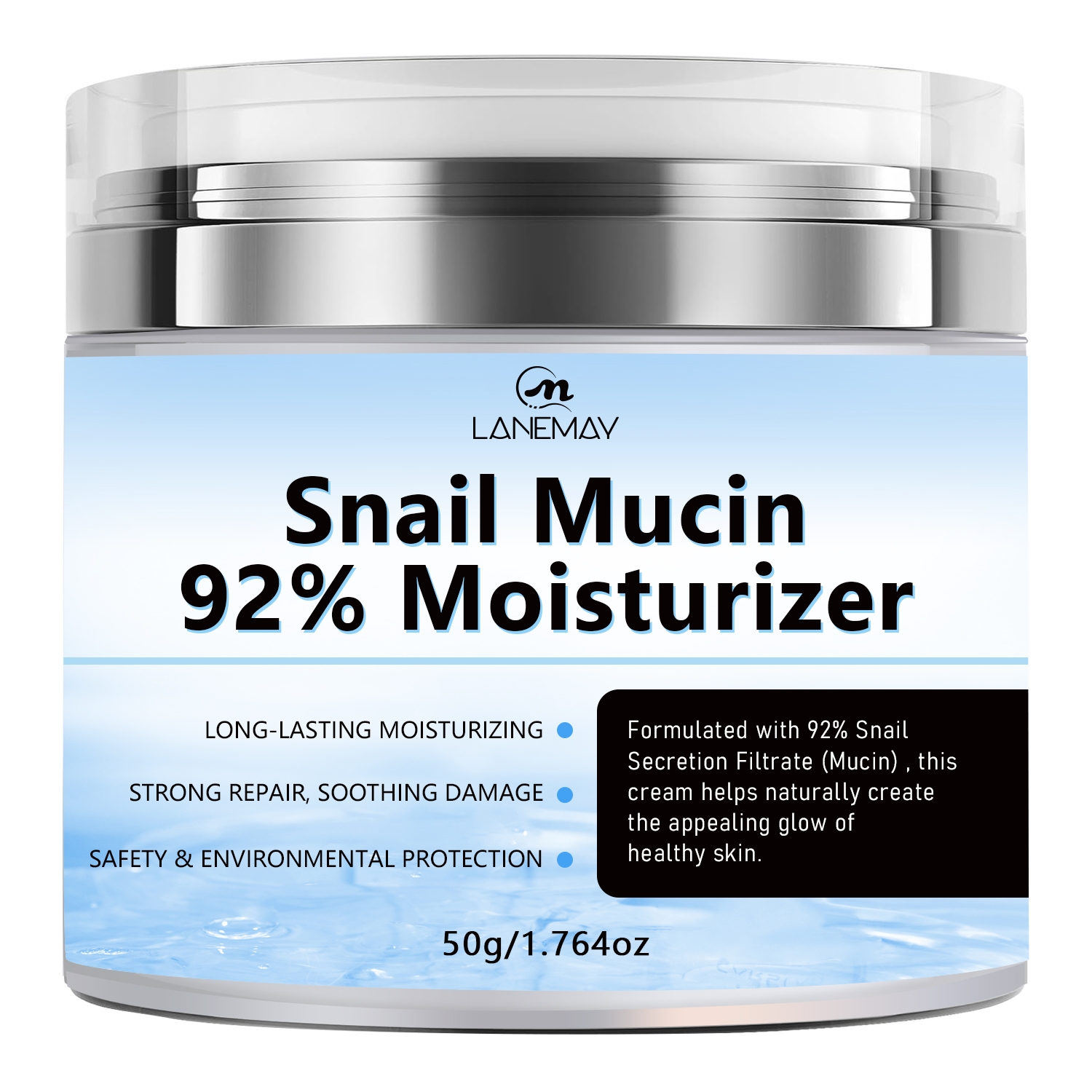 DRUG LABEL: Snail Mucin 92% Moisturizer
NDC: 84025-223 | Form: CREAM
Manufacturer: Guangzhou Yanxi Biotechnology Co., Ltd
Category: otc | Type: HUMAN OTC DRUG LABEL
Date: 20241021

ACTIVE INGREDIENTS: GLYCERIN 3 mg/50 g; CETYL ETHYLHEXANOATE 2 mg/50 g
INACTIVE INGREDIENTS: WATER

DOSAGE AND ADMINISTRATION

Apply to affected area twice per day on cleansed skin.

WARNINGS

Keep out of children

INACTIVE INGREDIENT

Aqua

INDICATIONS AND USAGE

For daily skin care

Keep out of chlidren

PURPOSE

Skin moisturizing